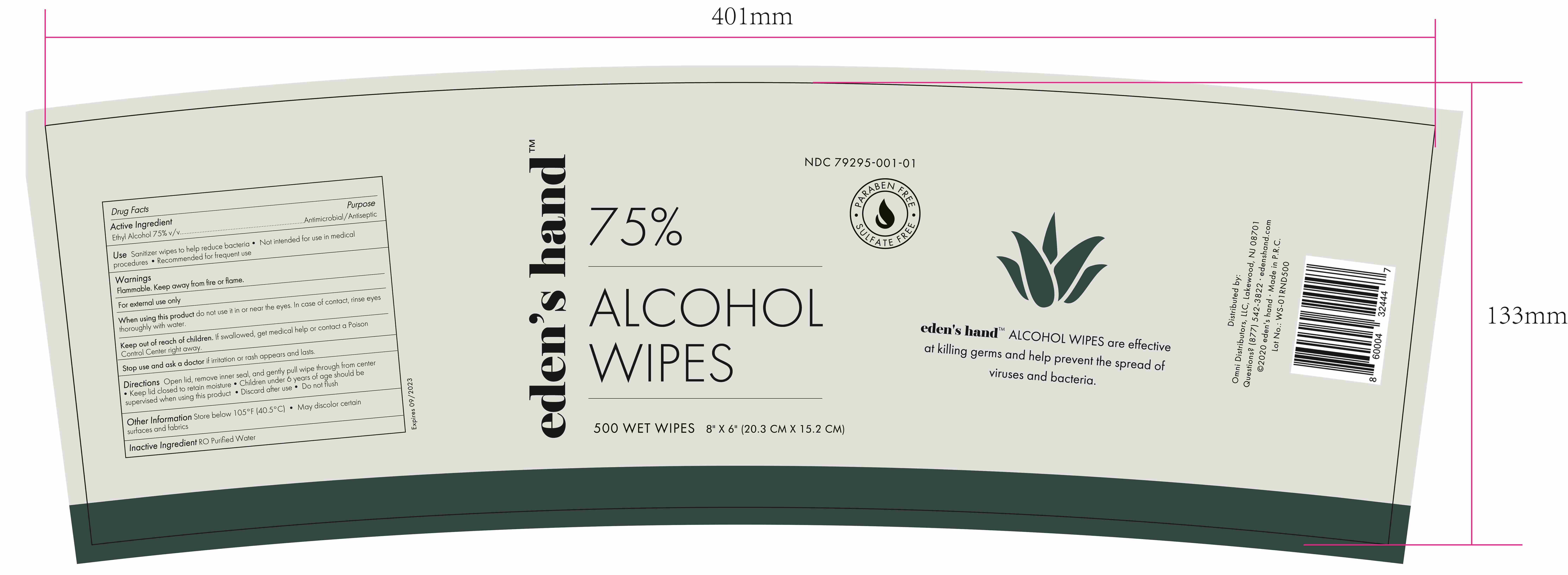 DRUG LABEL: ALCOHOL HAND WIPES
NDC: 55415-007 | Form: CLOTH
Manufacturer: JIANGSU MEIFAN BIOTECHNOLOGY CO., LTD.
Category: otc | Type: HUMAN OTC DRUG LABEL
Date: 20220422

ACTIVE INGREDIENTS: ALCOHOL 1600 mL/500 1
INACTIVE INGREDIENTS: WATER

DOSAGE AND ADMINISTRATION

Store below 105°F (40.5°C)

INACTIVE INGREDIENT

SPUNLACE NONWOVEN, PURIFIED WATER

INDICATIONS AND USAGE

Open lid, remove inner seal, and gently pull wipe through from center

ACTIVE INGREDIENT

ETHYL ALCOHOL

KEEP OUT OF REACH OF CHILDREN

Keep lid closed to retain moisture,Children under 6 years of age should besupervised when using this product

PURPOSE

Disinfection
Sterilization
No Rinseing

WARNINGS

Flammable. Keep away from fire or flame.For external use only